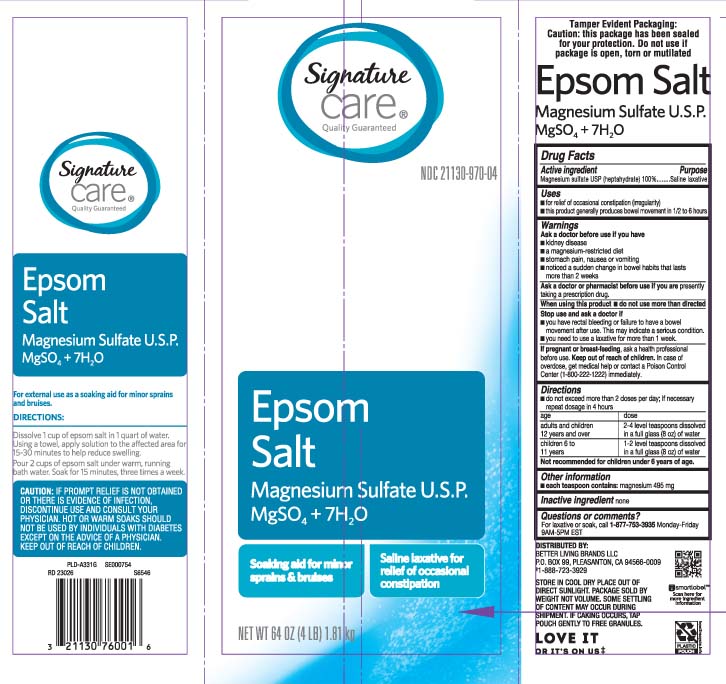 DRUG LABEL: Epsom Salt
NDC: 21130-970 | Form: GRANULE
Manufacturer: Safeway, Inc.
Category: otc | Type: HUMAN OTC DRUG LABEL
Date: 20250416

ACTIVE INGREDIENTS: MAGNESIUM SULFATE, UNSPECIFIED 1 g/1 g

Drug Facts

Active ingredient

Magnesium sulfate USP (heptahydrate) 100%

Purpose

Saline laxative

Uses

- for relief of occasional constipation (irregularity)
- this product generally produces bowel movement in 1/2 to 6 hours

Warnings

Ask a doctor before use if you have

- kidney disease
- a magnesium restricted diet
- stomach pain, nausea or vomiting
- noticed a sudden change in bowel habits that lasts more than 2 weeks

Ask a doctor or pharmacist before use if you are

presently taking a prescription drug.

When using this product

- do not use more than directed

Stop use and ask a doctor if

- you have rectal bleeding or failure to have a bowel movement after use. This may indicate a serious condition.
- you need to use a laxative for more than 1 week

If pregnancy or breast-feeding,

ask a health professional before use.

Keep out of reach of children.

In case of overdose, get medical help or contact a Poison Control Center (1-800-222-1222) immediately.

Directions

- do not exceed more than 2 doses per day; if necessary repeat dosage in 4 hours

age | dose
adults and children 12 years and older | 2-4 level teaspoons dissolved in a full glass (8oz) of water
children 6 to 11 years | 1-2 level teaspoons dissolved in a full glass (8oz) of water

Not recommended for children under 6 years of age.

Inactive Ingredients

None

Other information

- each teaspoon contains: magnesium 495 mg

Questions or comments?

For laxative or soak, call 1-877-753-3935 Monday- Friday 9AM-5PM EST

Principal Display Panel

EPSOM SALTS

Magnesium Sulfate U.S.P.

Mg SO4 + 7H2O

Soaking aid for minor sprains & bruises

Saline laxative for relief of occasional constipation

For external use as a soaking aid for minor sprains and bruises

CAUTION: IF PROMPT RELIEF IS NOT OBTAINED OR THERE IS EVIDENCE OF INFECTION. DISCONTINUE USE AND CONSULT YOUR PHYSICIAN. HOT OR WARM SOAKS SHOULD NOT BE USED BY INDIVIDUALS WITH DIABETES EXCEPT ON THE ADVISE OF A PHYSICIAN. KEEP OUT OF REACH OF CHILDREN.

STORE IN COOL DRY PLACE OUT OF DIRECT SUNLIGHT. PACKAGE SOLD BY WEIGHT NOT VOLUME. SOME SETTLING OF CONTENT MAY OCCUR DURING SHIPMENT. IF CAKING OCCURS, TAP POUCH GENTLE TO FREE GRANULES

NET WT OZ (LB) kg

Tamper Evident Packaging: Caution: this package has been sealed for your protection. Do not use if package is open, torn or mutilated

DISTRIBUTED BY:

BETTER LIVING BRANDS LLC

P.O. BOX 99, PLEASANTON, CA 94566-0009

Package Label

SIGNATURE CARE Epsom Salt